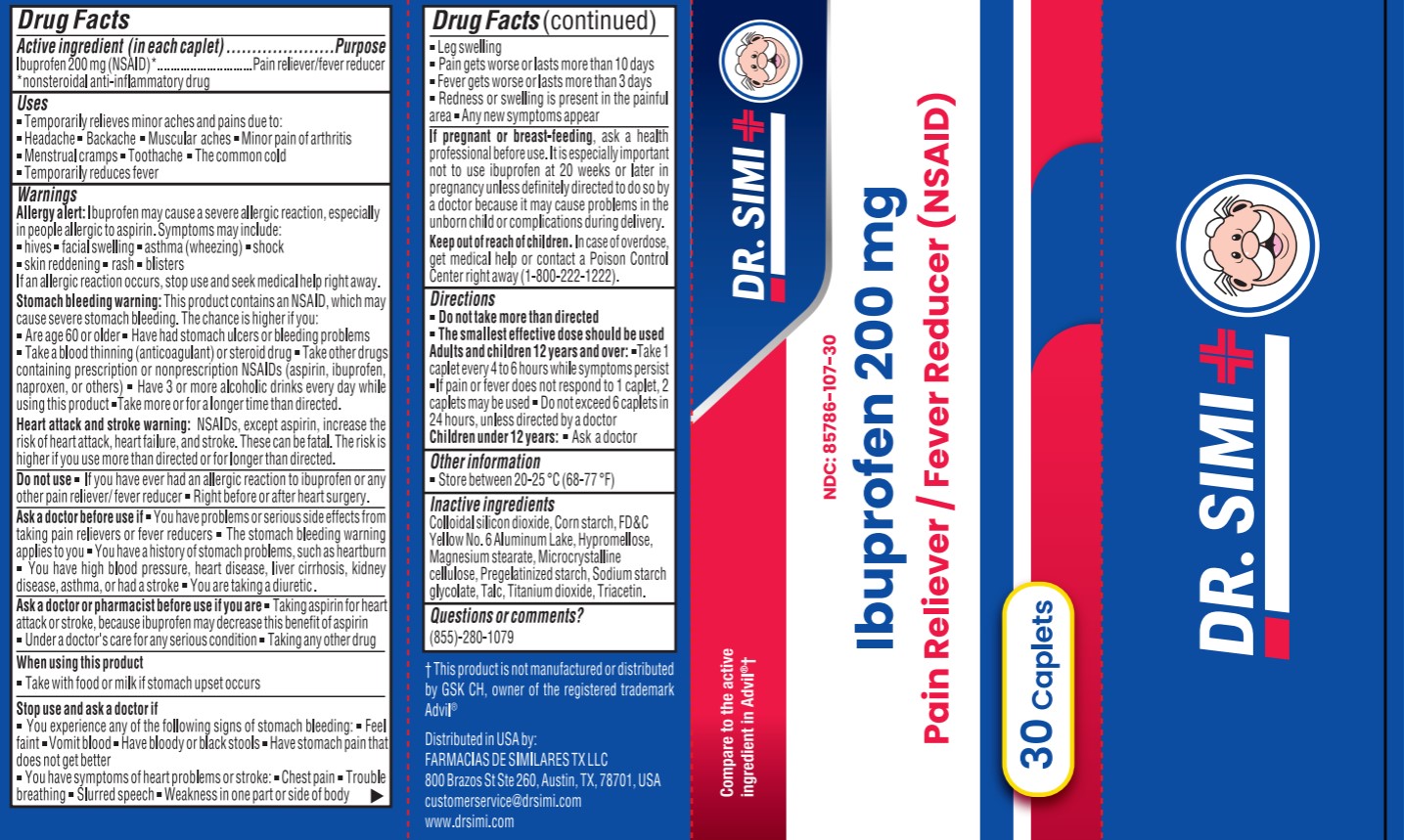 DRUG LABEL: IBUPROFEN 200 MG
NDC: 85786-107 | Form: TABLET, COATED
Manufacturer: Farmacias De Similares TX LLC
Category: otc | Type: HUMAN OTC DRUG LABEL
Date: 20260128

ACTIVE INGREDIENTS: IBUPROFEN 200 mg/1 1
INACTIVE INGREDIENTS: HYPROMELLOSES; MAGNESIUM STEARATE; TITANIUM DIOXIDE; MICROCRYSTALLINE CELLULOSE; SILICON DIOXIDE; STARCH, CORN; FD&C YELLOW NO. 6; SODIUM STARCH GLYCOLATE TYPE A POTATO; TALC; TRIACETIN

Active ingredient (in each caplet)

Ibuprofen 200 mg (NSAID)*
*nonsteroidal anti-inflammatory drug

Purpose

Pain reliever/fever reducer

Uses

. Temporarily relieves minor aches and pains due to:
- Headache - Backache - Muscular aches - Minor pain of arthritis - Menstrual cramps - Toothache - The common cold - Temporarily reduces fever

Warnings

Allergy alert: Ibuprofen may cause a severe allergic reaction, especially in people allergic to aspirin. Symptoms may include:

- hives - facial swelling - asthma (wheezing) - shock - skin reddening - rash - blisters
If an allergic reaction occurs, stop use and seek medical help right away.

Stomach bleeding warning: This product contains an NSAID, which may cause severe stomach bleeding. The chance is higher if you:
- Are age 60 or older - Have had stomach ulcers or bleeding problems - Take a blood thinning (anticoagulant) or steroid drug - Take other drugs containing prescription or nonprescription NSAIDs (aspirin, ibuprofen, naproxen, or others) - Have 3 or more alcoholic drinks every day while using this product -Take more or for a longer time than directed.

Heart attack and stroke warning: NSAIDs, except aspirin, increase the risk of heart attack, heart failure, and stroke. These can be fatal. The riskis higher if you use more than directed or for longer than directed.

Do not use

- If you have ever had an allergic reaction to ibuprofen or any other pain reliever/fever reducer - Right before or after heart surgery.

Ask a doctor before use if

- You have problems or serious side effects from taking pain relievers or fever reducers - The stomach bleeding warning applies to you - You have a history of stomach problems, such as heartburn - You have high blood pressure, heart disease, liver cirrhosis, kidney disease, asthma, or had a stroke - You are taking a diuretic.

Ask a doctor or pharmacist before use if you are

- Taking aspirin for heart attack or stroke, because ibuprofen may decrease this benefit of aspirin - Under a doctor's care for any serious condition - Taking any other drug

When using this product

- Take with food or milk if stomach upset occurs

Stop use and ask a doctor if

- You experience any of the following signs of stomach bleeding: - Feel faint - Vomit blood - Have bloody or black stools - Have stomach pain that does not get better

- You have symptoms of heart problems or stroke: - Chest pain - Trouble breathing - Slurred speech - Weakness in one part or side of body

- Leg swelling
- Pain gets worse or lasts more than 10 days
- Fever gets worse or lasts more than 3 days
- Redness or swelling is present in the painful area

- Any new symptoms appear

If pregnant or breast-feeding

ask a health professional before use. It is especially important not to use ibuprofen at 20 weeks or later in pregnancy unless definitely directed to do so by a doctor because it may cause problems in the unborn child or complications during delivery.

Keep out of reach of children

In case of overdose

get medical help or contact a Poison Control Center right away (1-800-222-1222).

Directions

- Do not take more than directed
- The smallest effective dose should be used
Adults and children 12 years and over: -Take 1 caplet every 4 to 6 hours while symptoms persist -If pain or fever does not respond to 1 caplet, 2 caplets may be used - Do not exceed 6 caplets in 24 hours, unless directed by a doctor
Children under 12 years: - Ask a doctor

Other information

Store between 20-25 ℃ (68-77°F)

Inactive ingredients

Colloidal silicon dioxide, Corn starch, FD&C Yellow No. 6 Aluminum Lake, Hypromellose, Magnesium stearate, Microcrystalline cellulose, Pregelatinized starch, Sodium starch glycolate, Talc, Titanium dioxide, Triacetin.

Questions or comments?

(855)-280-1079

t This product is not manufactured or distributed by GSK CH, owner of the registered trademark Advil®

Distributed in USA by:
FARMACIAS DE SIMILARES TXLLC
800 Brazos St Ste 260, Austin, TX, 78701, USA
customerservice@drsimi.com

PACKAGE LABEL

Dr. Simi

Compare to the active ingredient in Advil®

NDC: 85786-107-30
Ibuprofen 200 mg
Pain Reliever / Fever Reducer (NSAID)

30 caplets